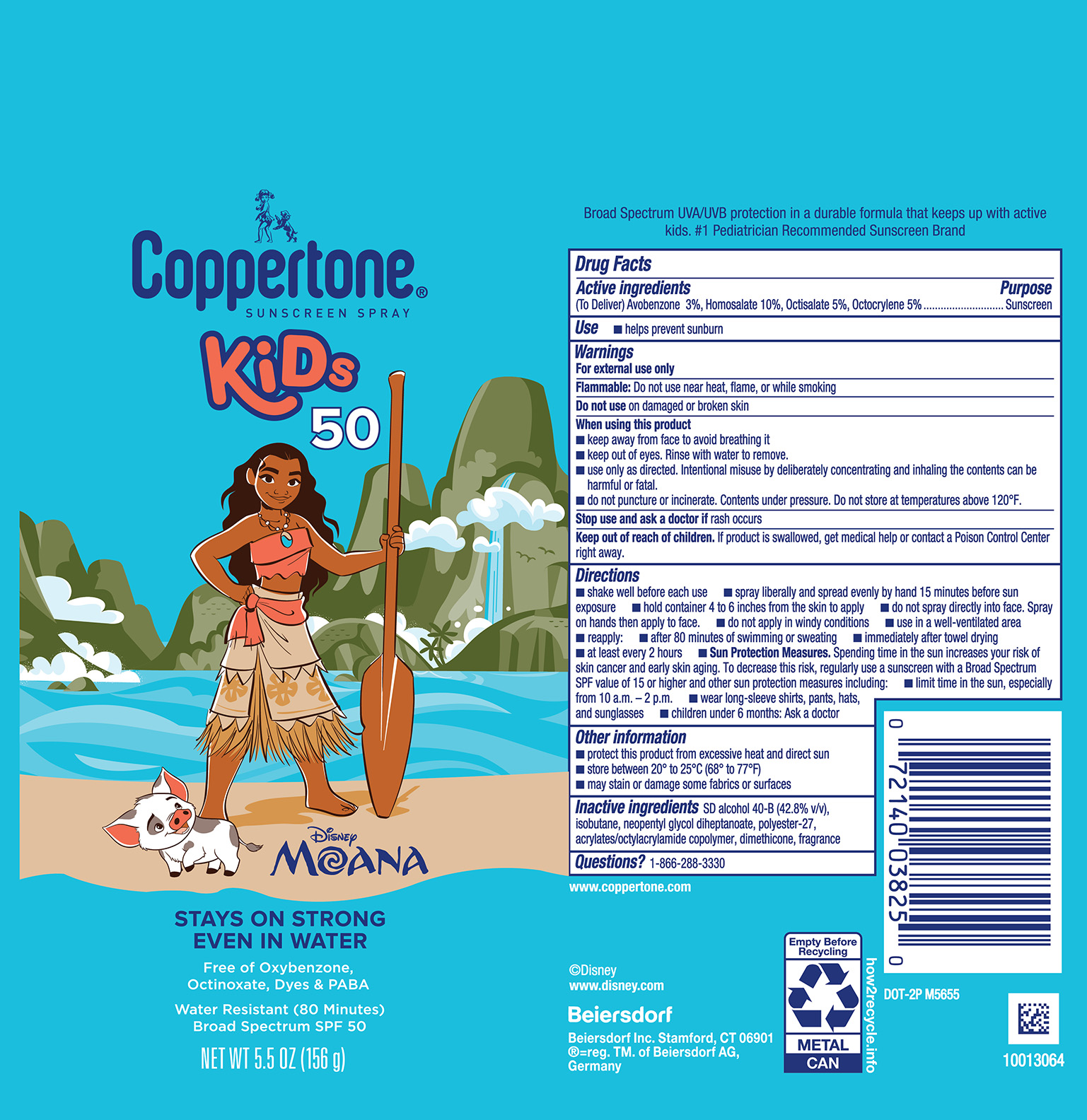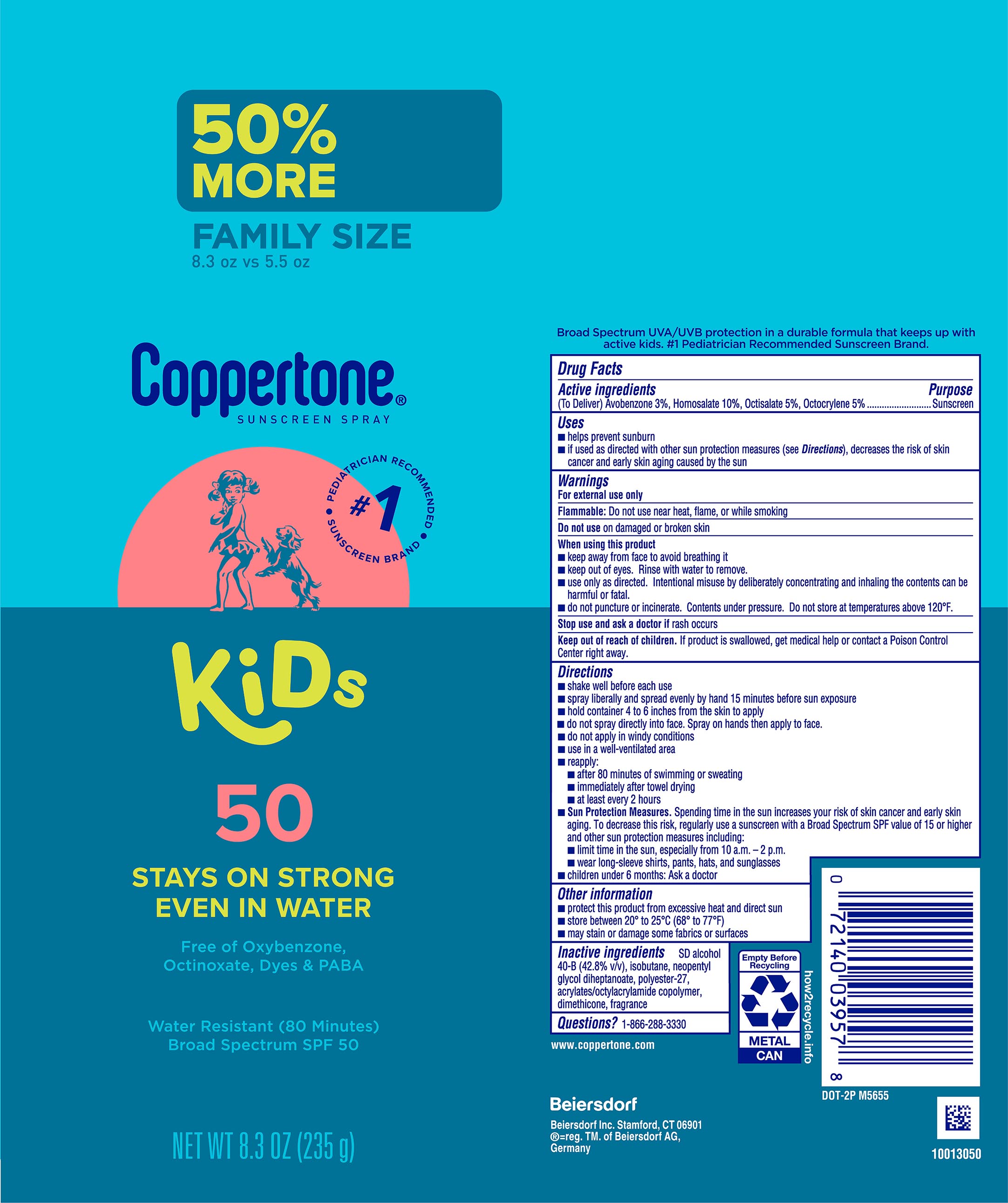 DRUG LABEL: Coppertone Kids Sunscreen SPF 50
NDC: 66800-4352 | Form: SPRAY
Manufacturer: Beiersdorf Inc.
Category: otc | Type: HUMAN OTC DRUG LABEL
Date: 20251231

ACTIVE INGREDIENTS: AVOBENZONE 3 g/100 g; OCTISALATE 5 g/100 g; OCTOCRYLENE 5 g/100 g; HOMOSALATE 10 g/100 g
INACTIVE INGREDIENTS: NEOPENTYL GLYCOL DIHEPTANOATE; DIMETHICONE; ASCORBYL PALMITATE; ALCOHOL; POLYESTER-7; ACRYLATES CROSSPOLYMER-6; FRAGRANCE FLORAL ORC0902236

Kids Sunscreen Spray SPF 50

Active ingredients

Avobenzone 3%, Homosalate 10%, Octisalate 5%, Octocrylene 5%

Purpose

Sunscreen

Uses

■ helps prevent sunburn

■ if used as directed with other sun protection measures (see Directions), decreases the risk of skin cancer and early skin aging caused by the sun

Warnings

For external use only

Flammable:Do not use near heat, flame, or while smoking

Do not useon damaged or broken skin

When using this product
■ keep away from face to avoid breathing it

■ keep out of eyes. Rinse with water to remove.

■ do not puncture or incinerate. Contents under pressure. Do not store at temperatures above 120˚F.

Stop use and ask a doctor ifrash occurs

Keep out of reach of children.If product is swallowed, get medical help or contact a Poison Control Center right away.

Directions

■ spray liberally and spread evenly by hand 15 minutes before sun exposure

■ hold container 4 to 6 inches from the skin to apply

■ do not spray directly into face. Spray on hands then apply to face.

■ do not apply in windy conditions

■ use in a well-ventilated area

■ reapply:

■ after 80 minutes of swimming or sweating

■ immediately after towel drying

■ at least every 2 hours

■ Sun Protection Measures. Spending time in the sun increases your risk of skin cancer and early skin aging. To decrease this risk, regularly use a sunscreen with a Broad Spectrum SPF value of 15 or higher and other sun protection measures including:

■ limit time in the sun, especially from 10 a.m. – 2 p.m.

■ wear long-sleeve shirts, pants, hats, and sunglasses

■ children under 6 months: Ask a doctor

Other information

■ protect this product from excessive heat and direct sun

■ avoid long-term storage above 40˚C (104˚F)

■ may stain or damage some fabrics or surfaces

Inactive ingredients

SD alcohol 40-B (73.8% v/v), neopentyl glycol diheptanoate, polyester-27, acrylates/octylacrylamide copolymer, dimethicone, fragrance, ascorbyl palmitate

Questions

1-866-288-3330

Principal Display Panel

#1 Pediatrician Recommended Brand

Coppertone®Sunscreen Spray

kids®

Stays on Strong Even in Water 50

Free of oxybenzone, octinoxate, dyes & PABA

Water Resistant (80 Minutes)

Broad Spectrum SPF 50

Net Wt 5.5 oz (156 g)